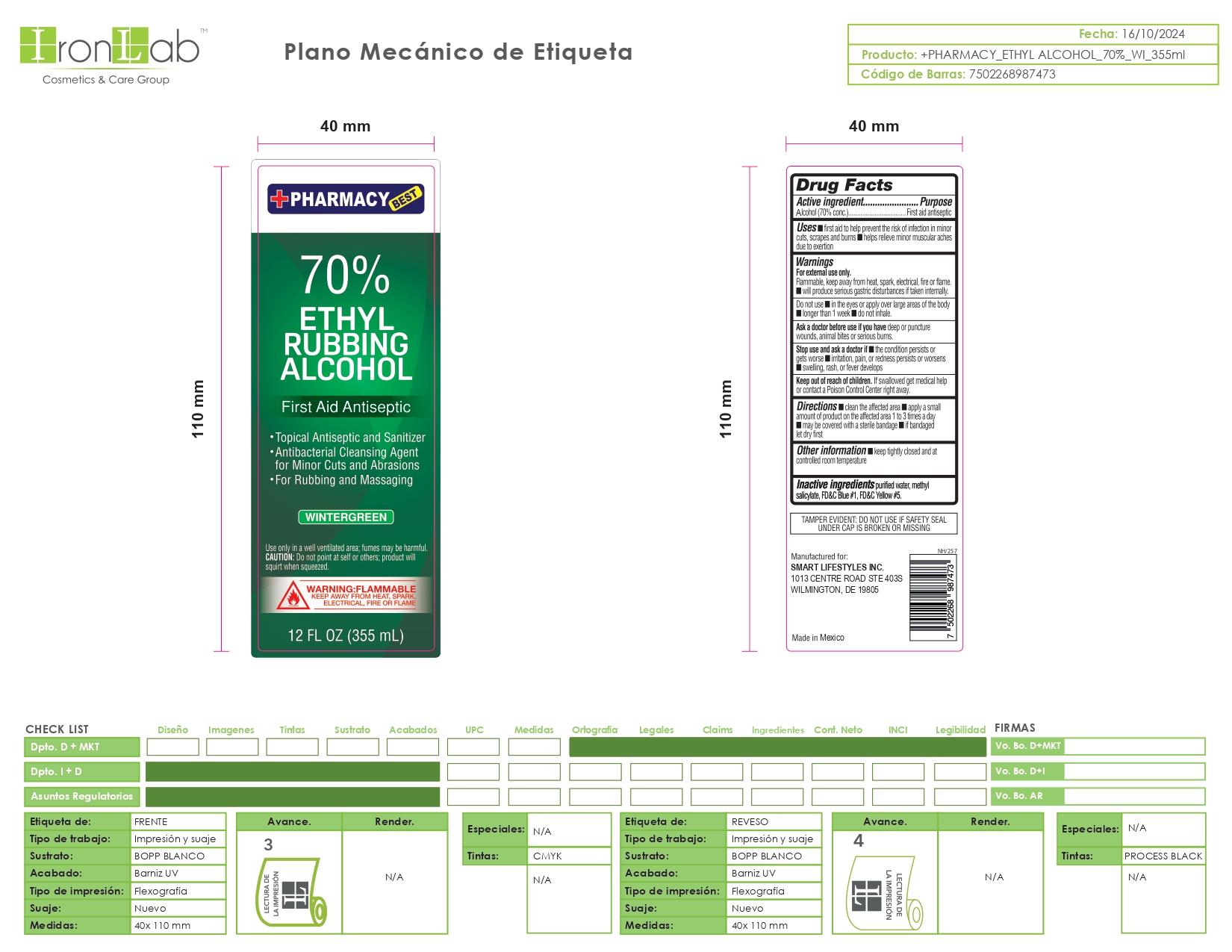 DRUG LABEL: 70 Alcohol Hand Sanitizer
NDC: 74375-060 | Form: LIQUID
Manufacturer: Iron Lab SA de CV
Category: otc | Type: HUMAN OTC DRUG LABEL
Date: 20260217

ACTIVE INGREDIENTS: ALCOHOL 70 mL/100 mL
INACTIVE INGREDIENTS: FD&C YELLOW NO. 5; METHYL SALICYLATE; WATER; FD&C BLUE NO. 1

Wintergreen 70 Iron Lab SA de CV

DOSAGE AND ADMINISTRATION

Thoroughly cover your hands with product and allow to dry without wiping. Children under 6 years of age should be supervised when using this product. Not recommended for infants.

INDICATIONS AND USAGE

To decrease bacteria on the skin that could cause disease. Recommended for repeated use.

INACTIVE INGREDIENT

purified water, methyl salicylate, FD&C Blue #1, FD&C Yellow #5

ACTIVE INGREDIENT

70% Ethyl Alcohol

WARNINGS

For external use only: hands. Flammable, Keep away from fire of flame.

ASK DOCTOR

Irritation or redness develops. Condition persist for more than 72 hours.

KEEP OUT OF REACH OF CHILDREN

If swallowed, get medical help or contact a Poison Control Center right away

OTHER SAFETY INFORMATION

Store below 105°F. May discolor some fabrics. Harmful to wood finishes and plastic

PURPOSE

Antiseptic Alcoho

WHEN USING

Keep out of eyes. In case of contact with eyes, flush thoroughly with water. Avoid contact with broken skin. Do not inhale or ingest.

PACKAGE LABEL

Wintergreen 70